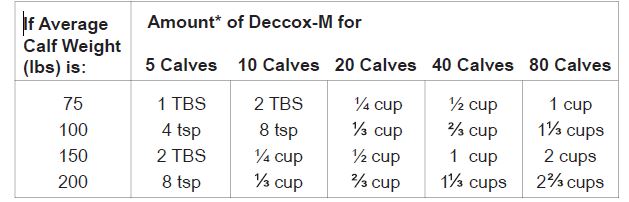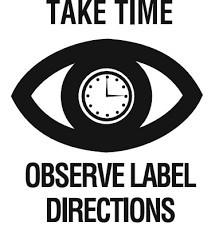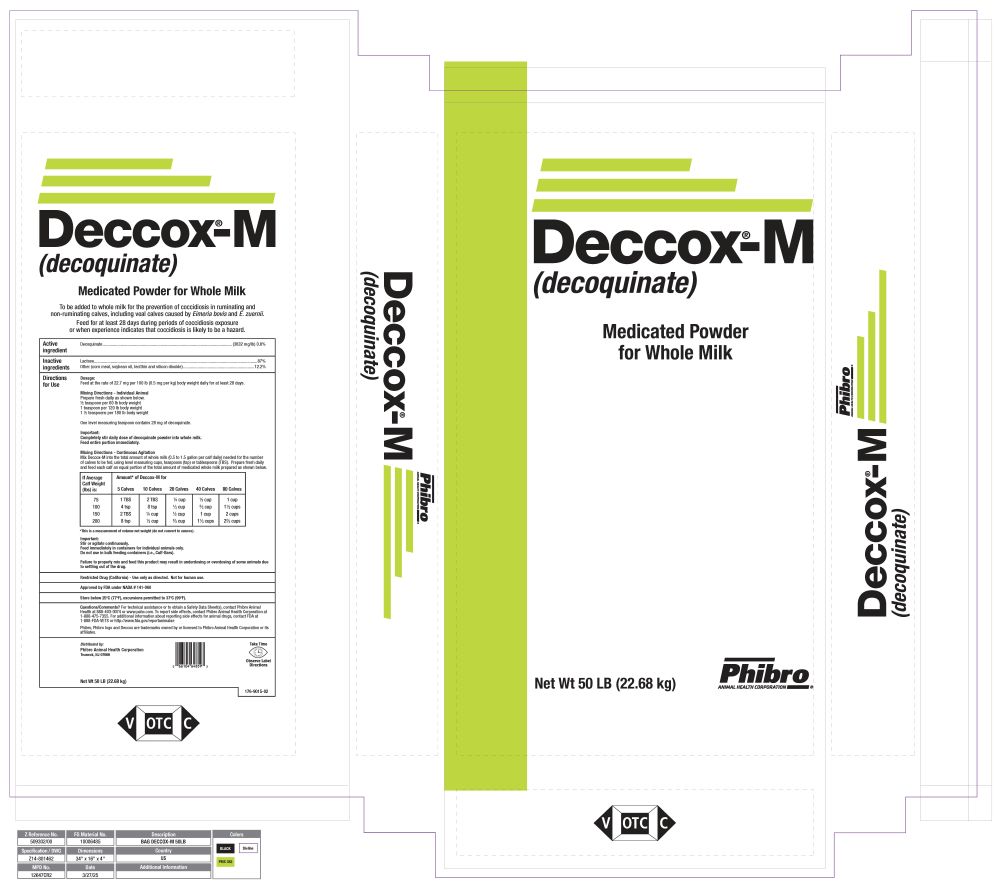 DRUG LABEL: Deccox
NDC: 66104-1510 | Form: POWDER
Manufacturer: Phibro Animal Health
Category: animal | Type: OTC TYPE A MEDICATED ARTICLE ANIMAL DRUG LABEL
Date: 20260120

ACTIVE INGREDIENTS: DECOQUINATE 3632 mg/0.45 kg
INACTIVE INGREDIENTS: SOYBEAN OIL; LECITHIN, SOYBEAN; SILICON DIOXIDE; LACTOSE, UNSPECIFIED FORM

Deccox®-M

None

Deccox®-M

(decoquinate)

Medicated Powder for Whole Milk

To be added to whole milk for the prevention of coccidiosis in ruminating and non-ruminating calves, including veal calves caused by Eimeria bovis and E. zuernii.

Feed for at least 28 days during periods of coccidiosis exposure or when experience indicates that coccidiosis is likely to be a hazard.

Active ingredient(s)

Decoquinate.......................(3632 mg/lb) 0.8%

Inactive ingredients

Lactose.............................................................................................................................87%

Other (corn meal, soybean oil, lecithin and silicon dioxide)...........................................12.2%

Directions for Use

Dosage:

Feed at the rate of 22.7 mg per 100 lb (0.5 mg per kg) body weight daily for at least 28 days.

Mixing Directions - Individual Animal

Prepare fresh daily as shown below.

1/2 teaspoon per 60 lb body weight

1 teaspoon per 120 lb body weight

1 1/2 teaspoons per 180 lb body weight

One level measuring teaspoon contains 28 mg of decoquinate.

Important:

Completely stir daily dose of decoquinate powder into whole milk.

Feed entire portion immediately.

Mixing Directions - Continuous Agitation

Mix Deccox-M into the total amount of whole milk (0.5 to 1.5 gallon per calf daily) needed for the number of calves to be fed, using level measuring cups, teaspoons (tsp) or tablespoons (TBS). Prepare fresh daily and feed each calf an equal portion of the total amount of medicated whole milk prepared as shown below.

Mixing Table

*This is a measurement of volume not weight (do not convert to ounces).

Important:

Stir or agitate continuously.

Feed immediately in containers for individual animals only.

Do not use in bulk feeding containers (i.e., Calf-Bars).

Failure to properly mix and feed this product may result in underdosing or overdosing of some animals due to settling out of the drug.

Other information

Restricted Drug (California) - Use only as directed. Not for human use.

Approved by FDA under NADA # 141-060

Storage

Store below 25oC (77oF), excursions permitted to 37oC (99oF).

Questions/Comments? For technical assistance or to obtain a Safety Data Sheet(s), contact Phibro Animal
Health at 888-403-0074 or www.pahc.com. To report side effects, contact Phibro Animal Health Corporation at
1-888-475-7355. For additional information about reporting side effects for animal drugs, contact FDA at
1-888-FDA-VETS or http://www.fda.gov/reportanimalae

Phibro, Phibro logo and Deccox are trademarks owned by or licensed to Phibro Animal Health Corporation or its affiliates.

Distributed by:

Phibro Animal Health Corporation

Teaneck, NJ 07666

Net Wt 50 LB (22.68 kg)

176-9015-02

Take Time

Principal Display Panel 50lb bag

Deccox M Label